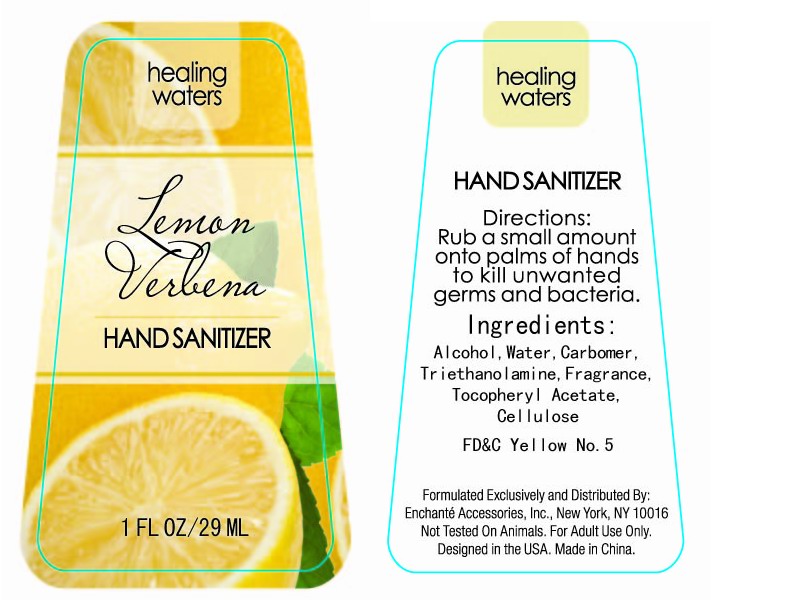 DRUG LABEL: Healing Waters Lemon Verbena Hand Sanitizer
NDC: 22100-003 | Form: LIQUID
Manufacturer: Ningbo Meiduo General Products Co., Ltd
Category: prescription | Type: HUMAN PRESCRIPTION DRUG LABEL
Date: 20100209

ACTIVE INGREDIENTS: ALCOHOL 60 g/100 g
INACTIVE INGREDIENTS: WATER 39.1992 g/100 g; CARBOMER HOMOPOLYMER TYPE A 0.2 g/100 g; TROLAMINE 0.2 g/100 g; .ALPHA.-TOCOPHEROL ACETATE, DL- 0.1 g/100 g; CELLULOSE, MICROCRYSTALLINE 0.1 g/100 g; FD&C YELLOW NO. 5 0.0008 g/100 g; LEMON 0.1 g/100 g; VERBENA 0.1 g/100 g

DRUG FACT

Directions:

Rub a small amount onto palms of hands to kill unwanted germs and bacteria

INACTIVE INGREDIENT

Ingredients:

Alcohol, Water, Carbomer, Triethanolamine, Fragrance, Tocopheryl Acetate, Cellulose, FD and C Yellow No. 5.

DESCRIPTION

Formulated Exclusively and Distributed by:

Enchante Accessories, Inc., New York, NY 10016

Not Tested on Animals. For Adult Use Only.

Designed in the USA. Made in China.

PACKAGE LABEL

pic